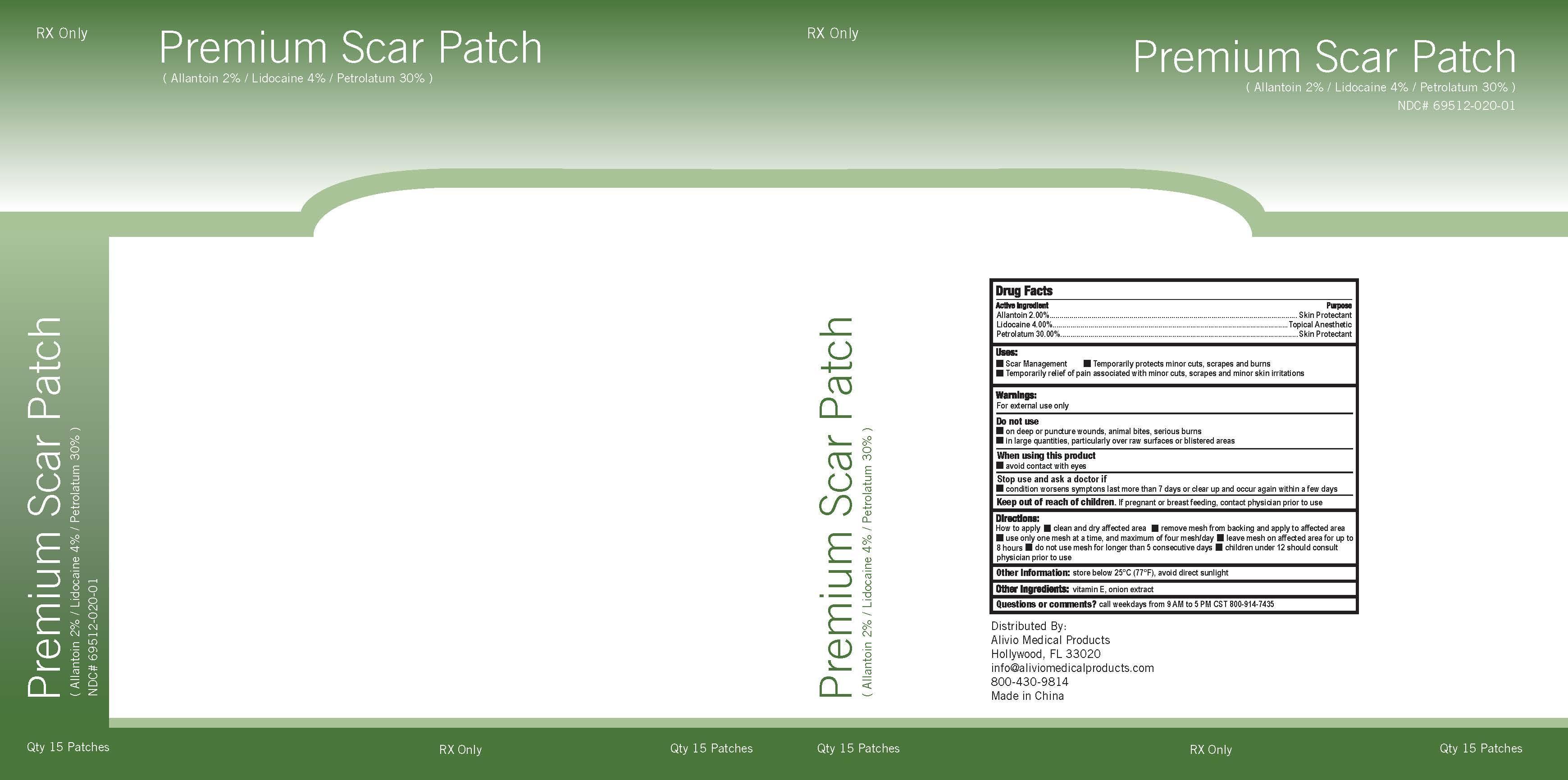 DRUG LABEL: Premium Scar Patch
NDC: 69512-020 | Form: PATCH
Manufacturer: Alivio Medical Products, LLC
Category: prescription | Type: HUMAN PRESCRIPTION DRUG LABEL
Date: 20150413

ACTIVE INGREDIENTS: ALLANTOIN 2 g/100 g; LIDOCAINE 5 g/100 g; PETROLATUM 30 g/100 g
INACTIVE INGREDIENTS: .ALPHA.-TOCOPHEROL; ONION

Drug Facts

Active Ingredient

Allantoin 2.00 %

Lidocaine 4.00 %

Pterolatum 30.00 %

Purpose

Allantoin 2.00 % ........ Skin Protectant

Lidocaine 4.00 % ........ Topical Anesthetic

Petrolatum 30.00 %..... Skin Protectant

Uses

- Scar Management - Temporarily protects minor cuts, scrapes and burns

-Temporary relief of pain associated with minor cuts, scrapes and minor skin irritations

Warnings

For external use only

Do not use

-on deep or puncture wounds, animal bites, serious burns

-in large quantities, particularly over raw surfaces or blistered areas

When using this product

-avoid contact with eyes

Stop use and ask a doctor if

-condition worsens symptoms last more than 7 days or clear up and occur again within a few days

Keep out of reach of children. If pregnant or breastfeeding, contact physician prior to use

Directions:

How to apply - clean and dry affected area -remove mesh from backing and apply to affected area

-use only one mesh at a time, and maximum of four mesh/day -leave mesh on affected area for up to

8 hours -do not use mesh for longer than 5 consecutive days -children under 12 should consult

physician prior to use

Other Information: store below 25C (77F), avoid direct sunlight

Questions or comments? call weekdays from 9 AM to 5 PM CST 800-914-7435